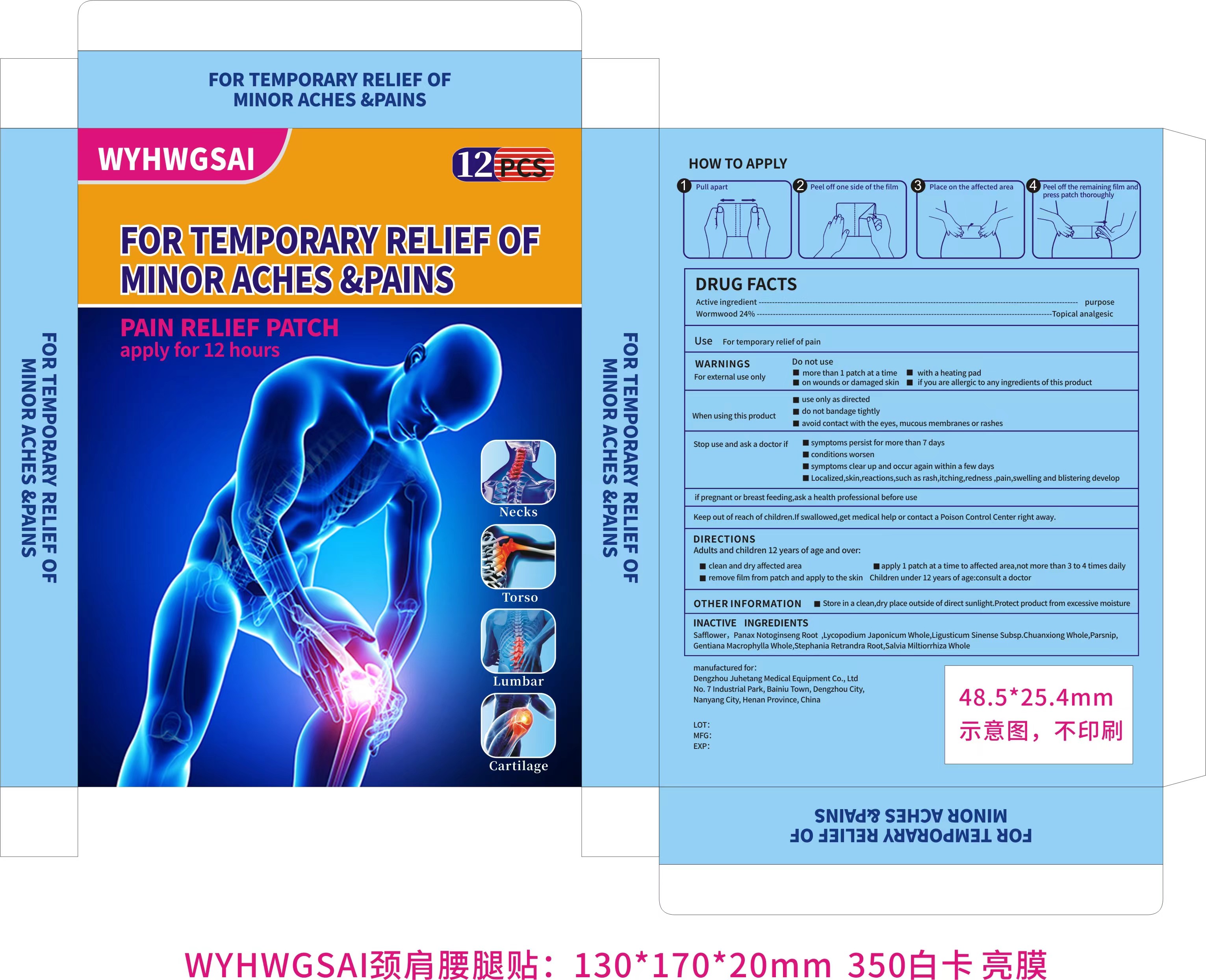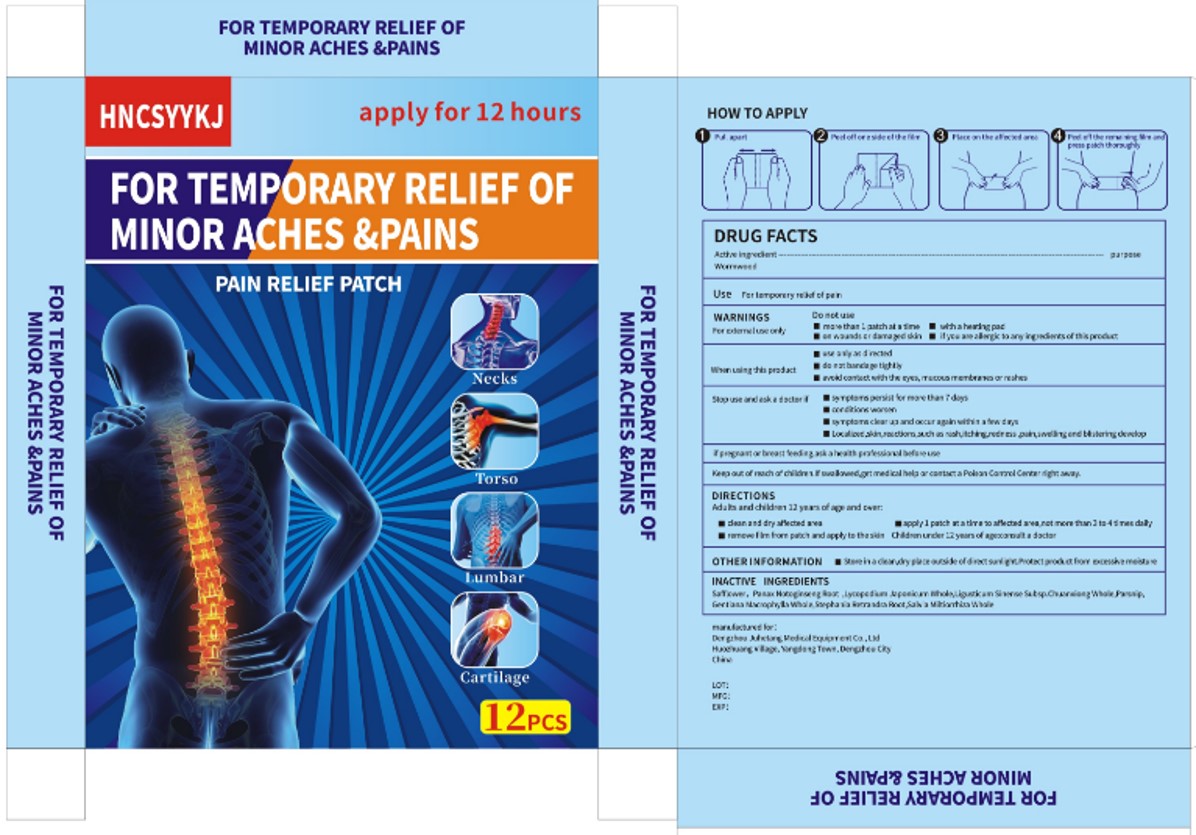 DRUG LABEL: Pain Relief Patch
NDC: 84171-101 | Form: PATCH
Manufacturer: Dengzhou Juhetang Medical Equipment Co., Ltd
Category: otc | Type: HUMAN OTC DRUG LABEL
Date: 20240307

ACTIVE INGREDIENTS: WORMWOOD 24 g/100 1
INACTIVE INGREDIENTS: LYCOPODIUM JAPONICUM WHOLE; PANAX NOTOGINSENG ROOT; GENTIANA MACROPHYLLA WHOLE; STEPHANIA TETRANDRA ROOT; SALVIA MILTIORRHIZA WHOLE; PARSNIP; SAFFLOWER; LIGUSTICUM SINENSE SUBSP. CHUANXIONG WHOLE

PAIN RELIEF PATCH

PAIN RELIEF PATCH

ACTIVE INGREDIENT

Wormwood 24%

PURPOSE

Topical analgesic

INDICATIONS AND USAGE

For temporary relief of pain

WARNINGS

For external use only

DO NOT USE

more than 1 patch at a time
with a heating pad
on wounds or damaged skin
if you are allergic to any ingredients of this product

WHEN USING

use only as directed
do not bandage tightly
avoid contact with the eyes, mucous membranes or rashes

STOP USE

symptoms persist for more than 7 days
conditions worsen
symptoms clear up and occur again within a few days
Localized,skin,reactions,such as rash,itching,redness ,pain,swelling and blistering develop

Keep out of reach of children.lf swallowed,get medical help or contact a Poison Control Center right away.

DOSAGE AND ADMINISTRATION

Adults and children 12 years of age and over:
clean and dry affected area
apply 1 patch at a time to affected area,not more than 3 to 4 times daily
remove film from patch and apply to the skin
Children under 12 years of age:consult a doctor

STORAGE AND HANDLING

Store in a clean,dry place outside of direct sunlight.Protect product from excessive moisture

INACTIVE INGREDIENT

Safflower
Panax Notoginseng Root
Lycopodium Japonicum Whole
Ligusticum Sinense Subsp.Chuanxiong Whole
Parsnip
Gentiana Macrophylla Whole
Stephania Retrandra Root
Salvia Miltiorrhiza Whole